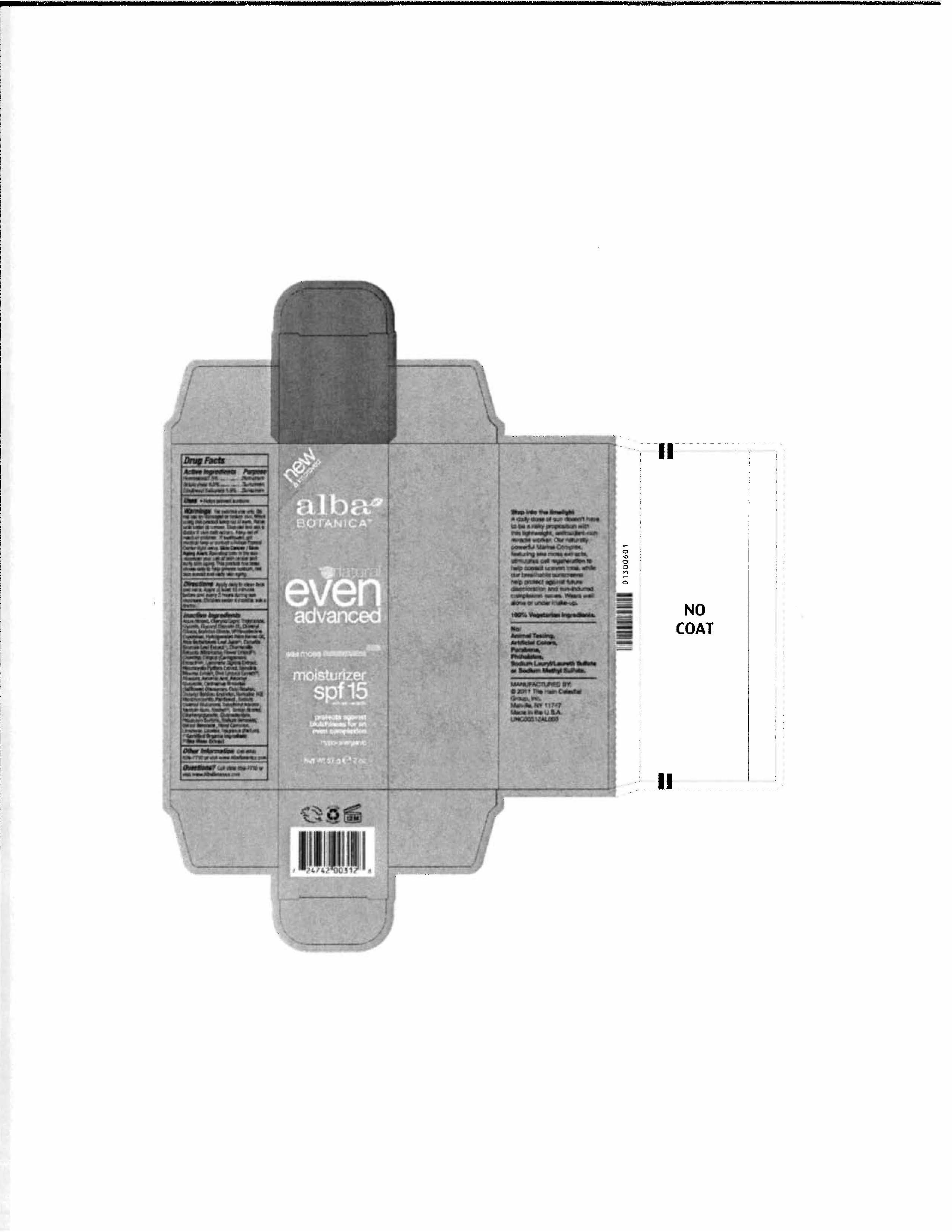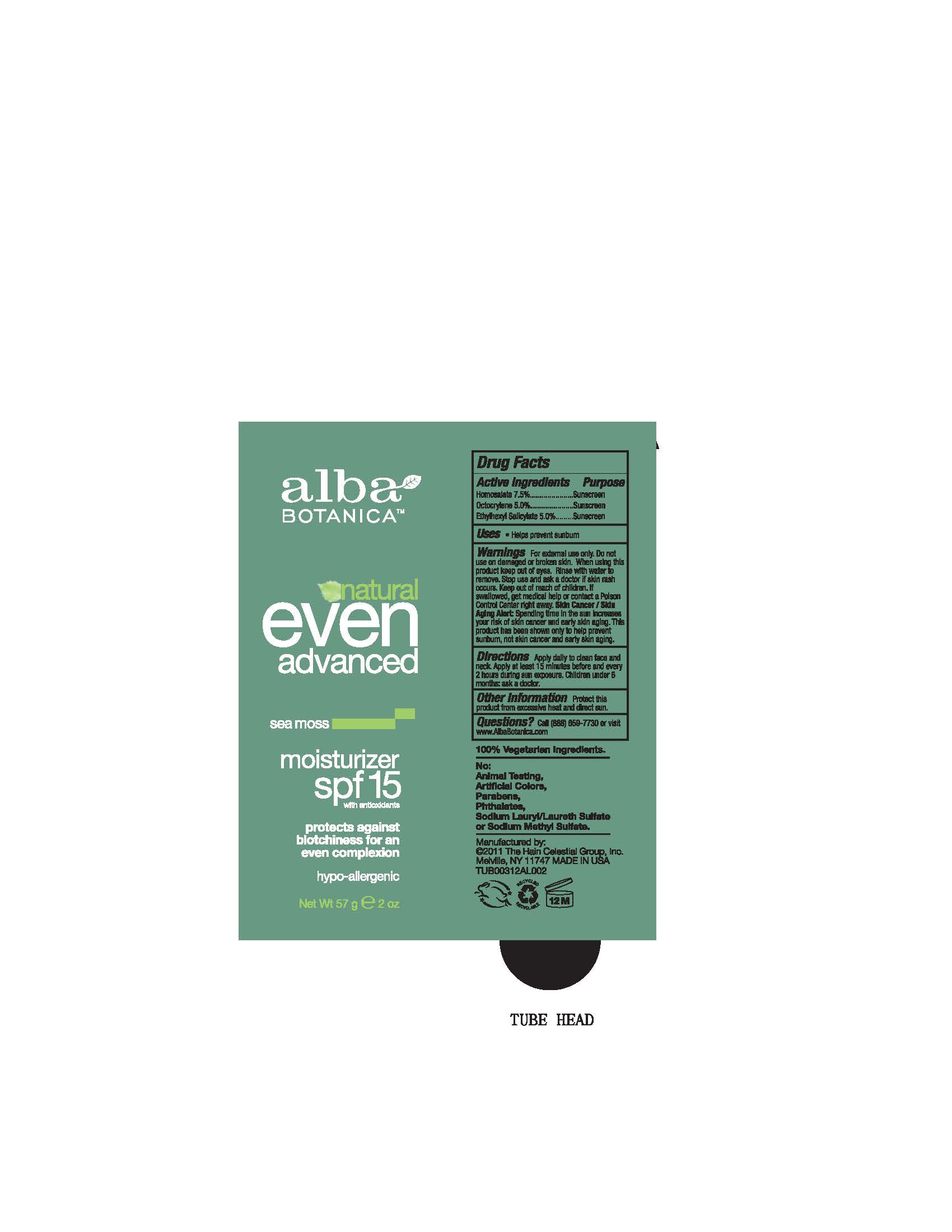 DRUG LABEL: Alba Botanica Natural Even Advanced Sea Moss Moisturizer SPF15
NDC: 61995-2312 | Form: LOTION
Manufacturer: The Hain Celestial Group, Inc.
Category: otc | Type: HUMAN OTC DRUG LABEL
Date: 20120518

ACTIVE INGREDIENTS: HOMOSALATE  7.5 g/100 g; OCTOCRYLENE 5.0 g/100 g; OCTISALATE  5.0 g/100 g
INACTIVE INGREDIENTS: WATER; GLYCERIN; MEDIUM-CHAIN TRIGLYCERIDES; GLYCERYL STEARATE SE; ALOE VERA LEAF; CHONDRUS CRISPUS ; GREEN TEA LEAF; CHAMOMILE ; CETEARYL OLIVATE ; SORBITAN OLIVATE; HYDROGENATED PALM KERNEL OIL; CETYL ALCOHOL ; LAMINARIA DIGITATA;  SPIRULINA MAXIMA; MACROCYSTIS PYRIFERA ; ULVA LACTUCA; .ALPHA.-TOCOPHEROL ACETATE; XANTHAN GUM ; ALCOHOL ; BENZYL ALCOHOL ; ALLANTOIN  ; POTASSIUM SORBATE ; SODIUM BENZOATE; ASCORBIC ACID ; ASCORBYL GLUCOSIDE; CARTHAMUS TINCTORIUS (SAFFLOWER) OLEOSOMES ; DIACETYL BOLDINE; ERYTHRITOL; HOMARINE HYDROCHLORIDE; MONTMORILLONITE; PANTHENOL; SODIUM STEAROYL GLUTAMATE; ETHYLHEXYLGLYCERIN; GLUCONOLACTONE; LIMONENE, (+)-; BENZYL BENZOATE; .ALPHA.-HEXYLCINNAMALDEHYDE; LINALOOL, (+/-)-

Drug Facts

ACTIVE INGREDIENT

Homosalate 7.5%

Octocrylene 5.0%

Ethylhexyl Salicylate 5.0%

PURPOSE

Sunscreen

INDICATIONS AND USAGE

- Helps prevent sunburn

WARNINGS

For external use only. Do not use on damaged or broken skin. When using this product keep out of eyes. Rinse with water to remove. Stop use and ask a doctor if skin rash occurs.

Keep out of reach of children. If swallowed, get medical help or contact a Poison Control Center right away

DOSAGE AND ADMINISTRATION

Apply daily to clean face and neck. Apply at least 15 minutes before and every 2 hours during sun exposure. Children under 6 months: ask a doctor.
Skin protection measures: Spending time in the sun increases your risk of skin cancer and early skin aging. This product has been shown only to help prevent sunburn, not skin cancer and early skin aging.

INACTIVE INGREDIENT

Aqua (Water), Caprylic/Capric Triglyceride, Glycerin, Glyceryl Stearate SE, Cetearyl Olivate, Sorbitan Olivate, VP/Hexadecene Copolymer, Hydrogenated Palm Kernel Oil, Aloe Barbadensis Leaf Juice (1), Chondrus Crispus (Sarrageenan) Extract (1) (2), Camellia Sinensis Leaf Extract (1), Chamomilla Recuitita (Matricaria) Flower Extract (1), Laminaria Digitata Extract, Macrocystis Purifera Extract, Spirulina Maxima Extract, Ulva Lactuca Extract (1), Cetyl Alcohol, Allantoin Ascorbic Acid, Ascorbyl Glucoside, Carthamus Tinctorius (Safflower) Oleosomes, Diacetyl Boldine, Erythritol, Homarine HCl, Montmorillonite, Panthenol ,Sodium Stearoyl Glutamate, Ethylhexylglycerin, Gluconolactone, Tocopheryl Acetate, Xanthan Gum, Alcohol (1), Benzyl Alcohol, Phenoxyethanol, Potassium Sorbate, Sodium Benzoate, Benzyl Benzoate, Hexyl Cinnamal, Limonene, Linalool, Fragrance (Parfum).
(1) Certified Organic Ingredient

(2) Sea Moss Extract

QUESTIONS

888-659-7730, www.AlbaBotanica.com